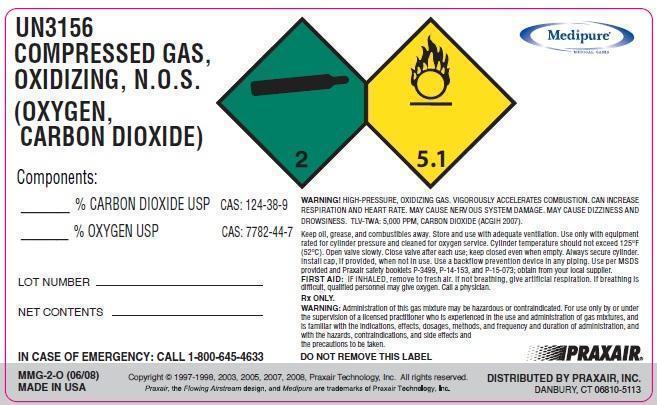 DRUG LABEL: Carbon Dioxide Oxygen Mix
NDC: 49972-008 | Form: GAS
Manufacturer: Praxair Distribution Southest LLC
Category: prescription | Type: HUMAN PRESCRIPTION DRUG LABEL
Date: 20130729

ACTIVE INGREDIENTS: CARBON DIOXIDE 300 mL/1 L; OXYGEN 700 mL/1 L

Carbon Dioxide/Oxygen mixture

PACKAGE LABEL

UN3156

COMPRESSED GAS,

OXIDIZING, N.O.S.

(OXYGEN, CARBON DIOXIDE)

% CARBON DIOXIDE USP CAS: 124-38-9

% OXYGEN USP CAS: 7782-44-7

NET CONTENTS

LOT NUMBER

WARNING! HIGH-PRESSURE, OXIDIZING GAS. VIGOROUSLY ACCELERATES COMBUSTION. CAN INCREASE RESPIRATION

AND HEART RATE. MAY CAUSE NERVOUS SYSTEM DAMAGE. MAY CAUSE DIZZINESS AND DROWSINESS.

TLV-TWA: 5,000 PPM CARBON DIOXIDE (ACGIH 2007).

Keep oil, grease, and combustibles away. Store and use with adequate ventilation. Use only with equipment rated for cylinder pressure and cleaned for oxygen service. Cylinder temperature should not exceed 125°F (52°C). Open valve slowly. Close valve after each use; keep closed even when empty. Always secure cylinder. Install cap, if provided, when not in use. Use a backflow prevention device in any piping. Use per MSDS provided and Praxair safety booklets P-3499, P-14-153, and

P-15-073; obtain from your local supplier.

FIRST AID: IF INHALED, remove to fresh air. If not breathing, give artificial respiration. If breathing is difficult, qualified personnel may give oxygen. Call a physician.

RX ONLY

WARNING! Administration of this gas mixture may be hazardous or contraindicated. For use only by or under the supervision of a licensed

practitioner who is experienced in the use and administration of gas mixtures and is familiar with the indications, effects, dosages, methods and

frequency and duration of administration, and with the hazards, contraindications, and side effects and the precautions to be taken.

Rx only IN CASE OF EMERGENCY CALL 1-800-645-4633

Copyright @ 1997-1998, 2003, 2005, 2007, 2008 Praxair Technology, Inc.

DO NOT REMOVE THIS LABEL MMG-2-0 (06/08)

Praxair, the flowing airstream design and Medipure are trademarks of Praxair Technology, Inc. DISTRIBUTED BY PRAXAIR, INC, DANBURY, CT 06810-5113